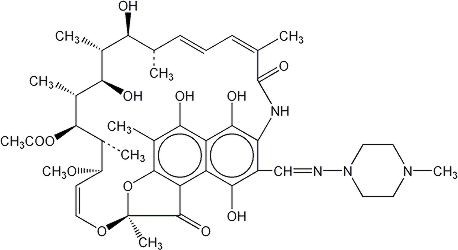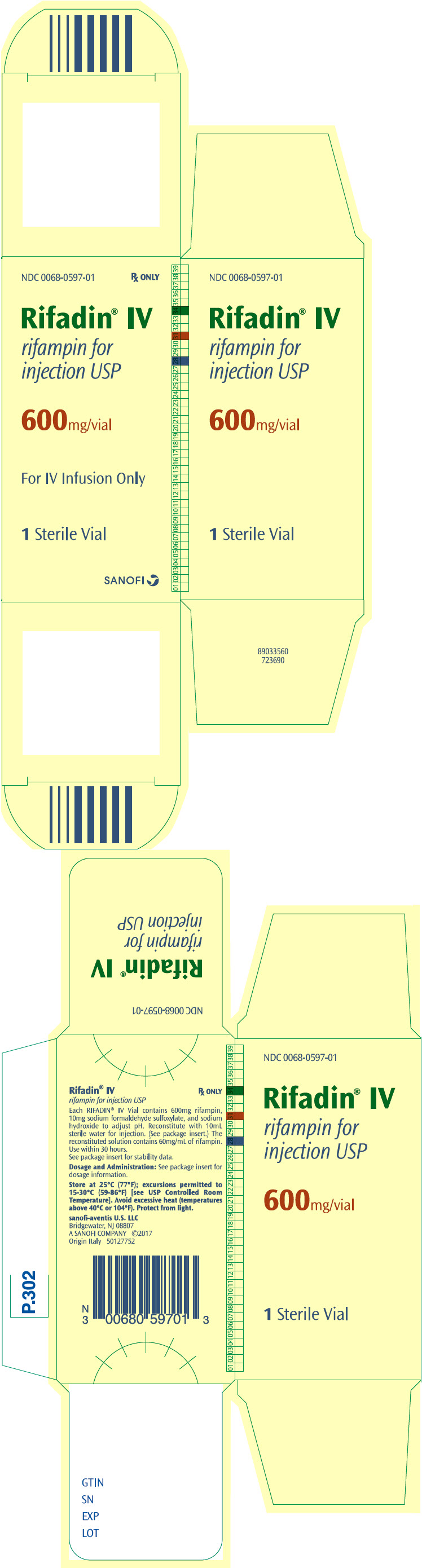 DRUG LABEL: Rifadin IV
NDC: 0068-0597 | Form: INJECTION, POWDER, LYOPHILIZED, FOR SOLUTION
Manufacturer: Sanofi-Aventis U.S. LLC
Category: prescription | Type: HUMAN PRESCRIPTION DRUG LABEL
Date: 20251017

ACTIVE INGREDIENTS: RIFAMPIN 600 mg/10 mL
INACTIVE INGREDIENTS: SODIUM FORMALDEHYDE SULFOXYLATE 10 mg/10 mL; SODIUM HYDROXIDE

RIFADIN®
(rifampin capsules USP)
and
RIFADIN® IV
(rifampin for injection USP)

To reduce the development of drug-resistant bacteria and maintain the effectiveness of RIFADIN (rifampin capsules USP) and RIFADIN IV (rifampin for injection USP) and other antibacterial drugs, rifampin should be used only to treat or prevent infections that are proven or strongly suspected to be caused by bacteria.

DESCRIPTION

RIFADIN (rifampin capsules USP) for oral administration contains 150 mg or 300 mg rifampin per capsule. The 150 mg and 300 mg capsules also contain, as inactive ingredients: corn starch, D&C Red No. 28, FD&C Blue No. 1, FD&C Red No. 40, gelatin, magnesium stearate, and titanium dioxide.

RIFADIN IV (rifampin for injection USP) contains rifampin 600 mg, sodium formaldehyde sulfoxylate 10 mg, and sodium hydroxide to adjust pH.

Rifampin is a semisynthetic antibiotic derivative of rifamycin SV. Rifampin is a red-brown crystalline powder very slightly soluble in water at neutral pH, freely soluble in chloroform, soluble in ethyl acetate and in methanol. Its molecular weight is 822.95 and its chemical formula is C43H58N4O12. The chemical name for rifampin is either:

3-[[(4-Methyl-1-piperazinyl)imino]methyl]rifamycin

or

5,6,9,17,19,21-hexahydroxy-23-methoxy-2,4,12,16,18,20,22–
heptamethyl-8-[N-(4-methyl-1-piperazinyl)formimidoyl]-2,7-(epoxypentadeca [1,11,13]trienimino)naphtho[2,1-b]furan-1,11(2H)-dione 21-acetate.

Its structural formula is:

CLINICAL PHARMACOLOGY

Oral Administration

Rifampin is readily absorbed from the gastrointestinal tract. Peak serum concentrations in healthy adults and pediatric populations vary widely from individual to individual. Following a single 600 mg oral dose of rifampin in healthy adults, the peak serum concentration averages 7 mcg/mL but may vary from 4 to 32 mcg/mL. Absorption of rifampin is reduced by about 30% when the drug is ingested with food.

Rifampin is widely distributed throughout the body. It is present in effective concentrations in many organs and body fluids, including cerebrospinal fluid. Rifampin is about 80% protein bound. Most of the unbound fraction is not ionized and, therefore, diffuses freely into tissues.

In healthy adults, the mean biological half-life of rifampin in serum averages 3.35±0.66 hours after a 600 mg oral dose, with increases up to 5.08±2.45 hours reported after a 900 mg dose. With repeated administration, the half-life decreases and reaches average values of approximately 2 to 3 hours. The half-life does not differ in patients with renal failure at doses not exceeding 600 mg daily, and, consequently, no dosage adjustment is required. The half-life of rifampin at a dose of 720 mg daily has not been established in patients with renal failure. Following a single 900 mg oral dose of rifampin in patients with varying degrees of renal insufficiency, the mean half-life increased from 3.6 hours in healthy adults to 5.0, 7.3, and 11.0 hours in patients with glomerular filtration rates of 30 to 50 mL/min, less than 30 mL/min, and in anuric patients, respectively. Refer to the WARNINGS section for information regarding patients with hepatic insufficiency.

After absorption, rifampin is rapidly eliminated in the bile, and an enterohepatic circulation ensues. During this process, rifampin undergoes progressive deacetylation so that nearly all the drug in the bile is in this form in about 6 hours. This metabolite has antibacterial activity. Intestinal reabsorption is reduced by deacetylation, and elimination is facilitated. Up to 30% of a dose is excreted in the urine, with about half of this being unchanged drug.

Intravenous Administration

After intravenous administration of a 300 or 600 mg dose of rifampin infused over 30 minutes to healthy male volunteers (n=12), mean peak plasma concentrations were 9.0±3.0 and 17.5±5.0 mcg/mL, respectively. Total body clearances after the 300 and 600 mg IV doses were 0.19±0.06 and 0.14±0.03 L/hr/kg, respectively. Volumes of distribution at steady state were 0.66±0.14 and 0.64±0.11 L/kg for the 300 and 600 mg IV doses, respectively. After intravenous administration of 300 or 600 mg doses, rifampin plasma concentrations in these volunteers remained detectable for 8 and 12 hours, respectively (see Table).

Plasma Concentrations (mean ± standard deviation, mcg/mL)
Rifampin Dosage IV | 30 min | 1 hr | 2 hr | 4 hr | 8 hr | 12 hr
300 mg | 8.9±2.9 | 4.9±1.3 | 4.0±1.3 | 2.5±1.0 | 1.1±0.6 | <0.4
600 mg | 17.4±5.1 | 11.7±2.8 | 9.4±2.3 | 6.4±1.7 | 3.5±1.4 | 1.2±0.6

Plasma concentrations after the 600 mg dose, which were disproportionately higher (up to 30% greater than expected) than those found after the 300 mg dose, indicated that the elimination of larger doses was not as rapid.

After repeated once-a-day infusions (3-hr duration) of 600 mg in patients (n=5) for 7 days, concentrations of IV rifampin decreased from 5.81±3.38 mcg/mL 8 hours after the infusion on day 1 to 2.6±1.88 mcg/mL 8 hours after the infusion on day 7.

Rifampin is widely distributed throughout the body. It is present in effective concentrations in many organs and body fluids, including cerebrospinal fluid. Rifampin is about 80% protein bound. Most of the unbound fraction is not ionized and therefore diffuses freely into tissues.

Rifampin is rapidly eliminated in the bile and undergoes progressive enterohepatic circulation and deacetylation to the primary metabolite, 25‑desacetyl-rifampin. This metabolite is microbiologically active. Less than 30% of the dose is excreted in the urine as rifampin or metabolites. Serum concentrations do not differ in patients with renal failure at a studied dose of 300 mg, and consequently, no dosage adjustment is required.

Pediatrics

Oral Administration

In one study, pediatric patients 6 to 58 months old were given rifampin suspended in simple syrup or as dry powder mixed with applesauce at a dose of 10 mg/kg body weight. Peak serum concentrations of 10.7±3.7 and 11.5±5.1 mcg/mL were obtained 1 hour after preprandial ingestion of the drug suspension and the applesauce mixture, respectively. After the administration of either preparation, the t½ of rifampin averaged 2.9 hours. It should be noted that in other studies in pediatric populations, at doses of 10 mg/kg body weight, mean peak serum concentrations of 3.5 mcg/mL to 15 mcg/mL have been reported.

Intravenous Administration

In pediatric patients 0.25 to 12.8 years old (n=12), the mean peak serum concentration of rifampin at the end of a 30-minute infusion of approximately 300 mg/m^2 was 25.9±1.3 mcg/mL; individual peak concentrations 1 to 4 days after initiation of therapy ranged from 11.7 to 41.5 mcg/mL; individual peak concentrations 5 to 14 days after initiation of therapy were 13.6 to 37.4 mcg/mL. The individual serum half-life of rifampin changed from 1.04 to 3.81 hours early in therapy to 1.17 to 3.19 hours 5 to 14 days after therapy was initiated.

In a pharmacokinetics (PK) study of 22 pediatric patients (median gestational age 27.5 weeks [range; 23–41 weeks] and median postnatal age (PNA) 7.5 days [range: 0–56 days]) receiving intravenous rifampin 10–20 mg/kg/day over 30 minutes, pediatric patients ≤7 days old had a median clearance of 0.09 L/kg/hr (range: 0.056–0.14 L/kg/hr) and a median area under the plasma drug concentration-time curve at infinity (AUC∞) of 105 mg*hr/L (range: 80172 mg*hr/L); pediatric patients >7 days PNA had a median clearance of 0.23 L/kg/hr (range: 0.14–0.32 L/kg/hr) and a median AUC∞ of 78 mg*hr/L (range: 51–170 mg*hr/L).

Based on PK modeling and simulation analyses, a dose of 12 mg/kg infused over 60 minutes once daily in pediatric patients ≤7 days PNA resulted in median (90% prediction interval) for maximum plasma concentration (Cmax) of 8.4 mcg/mL (range: 5.3 – 13.3 mcg/mL) and AUC∞ of 96.4 mg*hr/L (range: 64.5 – 141.6 mg*hr/L); in pediatric patients >7 days and < 90 days PNA a dose of 14 mg/kg infused over 60 minutes once daily resulted in a median (90% prediction interval) for Cmax of 9.6 mcg/mL (range: 6.l – 15.1 mcg/mL) and AUC∞ of 73.l mg*hr/L (range: 45.6 – 131.6 mg*hr/L). All simulated AUC∞ were within the range of AUC∞ values reported in other studies in adults treated for tuberculosis.

Mechanism of Action

Rifampin inhibits DNA-dependent RNA polymerase activity in susceptible Mycobacterium tuberculosis organisms. Specifically, it interacts with bacterial RNA polymerase but does not inhibit the mammalian enzyme.

Resistance

Organisms resistant to rifampin are likely to be resistant to other rifamycins.

In the treatment of both tuberculosis and the meningococcal carrier state (see INDICATIONS AND USAGE), the small number of resistant cells present within large populations of susceptible cells can rapidly become predominant. In addition, resistance to rifampin has been determined to occur as single-step mutations of the DNA-dependent RNA polymerase. Since resistance can emerge rapidly, appropriate susceptibility tests should be performed in the event of persistent positive cultures.

Activity in vitro and in vivo

Rifampin has bactericidal activity in vitro against slow and intermittently growing M. tuberculosis organisms.

Rifampin has been shown to be active against most isolates of the following microorganisms, both in vitro and in clinical infections (see INDICATIONS AND USAGE):

Aerobic Gram-Negative Microorganisms:
  Neisseria meningitidis

"Other" Microorganisms:
  Mycobacterium tuberculosis

The following in vitro data are available, but their clinical significance is unknown. At least 90% of the following bacteria exhibit an in vitro minimum inhibitory concentration (MIC) less than or equal to the susceptible breakpoint for rifampin against isolates of similar genus or organism group. However, the efficacy of rifampin in treating clinical infections caused by these bacteria has not been established in adequate and well-controlled clinical trials.

Aerobic Gram-Positive Microorganisms:
  Staphylococcus aureus (including Methicillin-Resistant S. aureus/MRSA)
  Staphylococcus epidermidis

Aerobic Gram-Negative Microorganisms:
  Haemophilus influenzae

"Other" Microorganisms:
  Mycobacterium leprae

β-lactamase production should have no effect on rifampin activity.

Susceptibility Testing

For specific information regarding susceptibility test criteria and associated test methods and quality control standards recognized by FDA for this drug, please see: www.fda.gov/STIC.

INDICATIONS AND USAGE

In the treatment of both tuberculosis and the meningococcal carrier state, the small number of resistant cells present within large populations of susceptible cells can rapidly become the predominant type. Bacteriologic cultures should be obtained before the start of therapy to confirm the susceptibility of the organism to rifampin and they should be repeated throughout therapy to monitor the response to treatment. Since resistance can emerge rapidly, susceptibility tests should be performed in the event of persistent positive cultures during the course of treatment. If test results show resistance to rifampin and the patient is not responding to therapy, the drug regimen should be modified.

Tuberculosis

Rifampin is indicated in the treatment of all forms of tuberculosis.

A three-drug regimen consisting of rifampin, isoniazid, and pyrazinamide is recommended in the initial phase of short-course therapy which is usually continued for 2 months. The Advisory Council for the Elimination of Tuberculosis, the American Thoracic Society, and Centers for Disease Control and Prevention recommend that either streptomycin or ethambutol be added as a fourth drug in a regimen containing isoniazid (INH), rifampin, and pyrazinamide for initial treatment of tuberculosis unless the likelihood of INH resistance is very low. The need for a fourth drug should be reassessed when the results of susceptibility testing are known. If community rates of INH resistance are currently less than 4%, an initial treatment regimen with less than four drugs may be considered.

Following the initial phase, treatment should be continued with rifampin and isoniazid for at least 4 months. Treatment should be continued for longer if the patient is still sputum or culture positive, if resistant organisms are present, or if the patient is HIV positive.

RIFADIN IV is indicated for the initial treatment and retreatment of tuberculosis when the drug cannot be taken by mouth.

Meningococcal Carriers

Rifampin is indicated for the treatment of asymptomatic carriers of Neisseria meningitidis to eliminate meningococci from the nasopharynx. Rifampin is not indicated for the treatment of meningococcal infection because of the possibility of the rapid emergence of resistant organisms. (See WARNINGS.)

Rifampin should not be used indiscriminately, and, therefore, diagnostic laboratory procedures, including serotyping and susceptibility testing, should be performed for establishment of the carrier state and the correct treatment. So that the usefulness of rifampin in the treatment of asymptomatic meningococcal carriers is preserved, the drug should be used only when the risk of meningococcal disease is high.

To reduce the development of drug-resistant bacteria and maintain the effectiveness of rifampin and other antibacterial drugs, rifampin should be used only to treat or prevent infections that are proven or strongly suspected to be caused by susceptible bacteria. When culture and susceptibility information are available, they should be considered in selecting or modifying antibacterial therapy. In the absence of such data, local epidemiology and susceptibility patterns may contribute to the empiric selection of therapy.

CONTRAINDICATIONS

RIFADIN is contraindicated in patients with a history of hypersensitivity to rifampin or any of the components, or to any of the rifamycins. (See WARNINGS.)

Rifampin is contraindicated in patients who are also receiving ritonavir-boosted saquinavir due to an increased risk of severe hepatocellular toxicity. (See PRECAUTIONS, Drug Interactions.)

Rifampin is contraindicated in patients who are also receiving atazanavir, darunavir, fosamprenavir, saquinavir, or tipranavir due to the potential of rifampin to substantially decrease plasma concentrations of these antiviral drugs, which may result in loss of antiviral efficacy and/or development of viral resistance.

Rifampin is contraindicated in patients receiving praziquantel since therapeutically effective blood levels of praziquantel may not be achieved. In patients receiving rifampin who need immediate treatment with praziquantel alternative agents should be considered. However, if treatment with praziquantel is necessary, rifampin should be discontinued 4 weeks before administration of praziquantel. Treatment with rifampin can then be restarted one day after completion of praziquantel treatment.

Rifampin is contraindicated in patients receiving lurasidone. Concomitant use of lurasidone with strong CYP3A4 inducers (e.g., rifampin) decreased the exposure of lurasidone compared to the use of lurasidone alone. (See PRECAUTIONS, Drug Interactions).

WARNINGS

Hepatotoxicity of hepatocellular, cholestatic, and mixed patterns has been reported in patients treated with rifampin. Severity ranged from asymptomatic elevations in liver enzymes, isolated jaundice/hyperbilirubinemia, symptomatic self-limited hepatitis to fulminant liver failure and death. Severe hepatic dysfunction including fatalities were reported in patients with liver disease and in patients taking rifampin with other hepatotoxic agents.

Monitor for symptoms and clinical/laboratory signs of liver injury, especially if treatment is prolonged or given with other hepatotoxic drugs. Patients with impaired liver function should be given rifampin only in cases of necessity and then under strict medical supervision. In these patients, careful monitoring of liver function should be done prior to therapy and then every 2 to 4 weeks during therapy. If signs of hepatic damage occur or worsen, discontinue rifampin.

Rifampin has enzyme-inducing properties, including induction of delta amino levulinic acid synthetase. Isolated reports have associated porphyria exacerbation with rifampin administration.

The possibility of rapid emergence of resistant meningococci restricts the use of RIFADIN to short-term treatment of the asymptomatic carrier state. RIFADIN is not to be used for the treatment of meningococcal disease.

Systemic hypersensitivity reactions were reported with RIFADIN administration. Signs and symptoms of hypersensitivity reactions may include fever, rash, urticaria, angioedema, hypotension, acute bronchospasm, conjunctivitis, thrombocytopenia, neutropenia, elevated liver transaminases or flu-like syndrome (weakness, fatigue, muscle pain, nausea, vomiting, headache, chills, aches, itching, sweats, dizziness, shortness of breath, chest pain, cough, syncope, palpitations). Manifestations of hypersensitivity, such as fever, lymphadenopathy or laboratory abnormalities (including eosinophilia, liver abnormalities) may be present even though rash is not evident. Monitor patients receiving RIFADIN for signs and/or symptoms of hypersensitivity reactions. If these signs or symptoms occur, discontinue RIFADIN and administer supportive measures.

Cases of severe cutaneous adverse reactions (SCAR) such as Stevens-Johnson syndrome (SJS), toxic epidermal necrolysis (TEN), acute generalized exanthematous pustulosis (AGEP), and drug reaction with eosinophilia and systemic symptoms (DRESS) syndrome have been reported with rifampin. If symptoms or signs of severe cutaneous adverse reactions develop, discontinue RIFADIN immediately and institute appropriate therapy.

Rifampin may cause vitamin K–dependent coagulation disorders and bleeding (see ADVERSE REACTIONS). Monitor coagulation tests during rifampin treatment (prothrombin time and other coagulation tests) in patients at risk of vitamin K deficiency (such as those with chronic liver disease, poor nutritional status, on prolonged antibacterial drugs or anticoagulants). Consider discontinuation of RIFADIN if abnormal coagulation tests and/or bleeding occur. Supplemental vitamin K administration should be considered when appropriate.

Pulmonary toxicity manifested as interstitial lung disease (including, but not limited to, pneumonitis, hypersensitivity pneumonitis, eosinophilic pneumonia, pulmonary infiltrates, and organizing pneumonia) has been reported with rifampin treatment. Pulmonary toxicity could be fatal. If symptoms or signs of severe pulmonary toxicity (including respiratory failure, pulmonary fibrosis, and acute respiratory distress syndrome) develop, discontinue RIFADIN immediately and initiate appropriate treatment.

Postmarketing reports suggest that concomitant administration of high doses of cefazolin and rifampin may prolong the prothrombin time, leading to severe vitamin K–dependent coagulation disorders that may be life-threatening or fatal. Avoid concomitant use of cefazolin and rifampin in patients at increased risk for bleeding. If no alternative treatment options are available, closely monitor prothrombin time and other coagulation tests, and administer vitamin K as indicated.

Postmarketing cases of paradoxical drug reaction (recurrence or appearance of new symptoms, physical and radiological signs in a patient who had previously shown improvement with appropriate antimycobacterial treatment, in the absence of disease relapse, poor treatment compliance, drug resistance, side effects of treatment, or secondary infection/diagnosis) have been reported with RIFADIN (see ADVERSE REACTIONS). Paradoxical drug reactions are often transient and should not be misinterpreted as failure to respond to treatment. If worsening of symptoms or signs occurs during antimycobacterial treatment, consider paradoxical drug reaction in the differential diagnosis, monitor, or treat accordingly.

Cases of thrombotic microangiopathy (TMA), including thrombotic thrombocytopenic purpura and hemolytic uremia syndrome, some fatal, have been reported with rifampin. Discontinue RIFADIN if clinical symptoms and laboratory findings consistent with TMA occur. The findings of unexplained thrombocytopenia and anemia should prompt further evaluation and consideration of the diagnosis of TMA.

PRECAUTIONS

General

RIFADIN should be used with caution in patients with a history of diabetes mellitus, as diabetes management may be more difficult.

Prescribing rifampin in the absence of a proven or strongly suspected bacterial infection or a prophylactic indication is unlikely to provide benefit to the patient and increases the risk of the development of drug-resistant bacteria.

For the treatment of tuberculosis, rifampin is usually administered on a daily basis. Doses of rifampin greater than 600 mg given once or twice weekly have resulted in a higher incidence of adverse reactions, including the "flu syndrome" (fever, chills, and malaise), hematopoietic reactions (leukopenia, thrombocytopenia, or acute hemolytic anemia), cutaneous, gastrointestinal, and hepatic reactions, shortness of breath, shock, anaphylaxis, and renal failure. Recent studies indicate that regimens using twice-weekly doses of rifampin 600 mg plus isoniazid 15 mg/kg are much better tolerated.

Rifampin is not recommended for intermittent therapy; the patient should be cautioned against intentional or accidental interruption of the daily dosage regimen since rare renal hypersensitivity reactions have been reported when therapy was resumed in such cases.

Rifampin has enzyme induction properties that can enhance the metabolism of endogenous substrates including adrenal hormones, thyroid hormones, and vitamin D. Rifampin and isoniazid have been reported to alter vitamin D metabolism. In some cases, reduced levels of circulating 25-hydroxy vitamin D and 1,25-dihydroxy vitamin D have been accompanied by reduced serum calcium and phosphate, and elevated parathyroid hormone.

RIFADIN IV

For intravenous infusion only. Must not be administered by intramuscular or subcutaneous route. Avoid extravasation during injection: local irritation and inflammation due to extravascular infiltration of the infusion have been observed. If these occur, the infusion should be discontinued and restarted at another site.

Information for Patients

Patients should be counseled that antibacterial drugs including rifampin should only be used to treat bacterial infections. They do not treat viral infections (e.g., the common cold). When rifampin is prescribed to treat a bacterial infection, patients should be told that although it is common to feel better early in the course of therapy, the medication should be taken exactly as directed. Skipping doses or not completing the full course of therapy may (1) decrease the effectiveness of the immediate treatment and (2) increase the likelihood that bacteria will develop resistance and will not be treatable by rifampin or other antibacterial drugs in the future.

The patient should be told that rifampin may produce a discoloration (yellow, orange, red, brown) of the teeth, urine, sweat, sputum, and tears, and the patient should be forewarned of this. Soft contact lenses may be permanently stained.

Rifampin is a well characterized and potent inducer of drug metabolizing enzymes and transporters and might therefore decrease or increase concomitant drug exposure and impact safety and efficacy (see DRUG INTERACTIONS). Therefore, patients should be advised not to take any other medication without medical advice.

The patient should be advised that the reliability of oral or other systemic hormonal contraceptives may be affected; consideration should be given to using alternative contraceptive measures.

Patients should be instructed to take rifampin either 1 hour before or 2 hours after a meal with a full glass of water.

Patients should be instructed to notify their physician immediately if they experience any of the following: rash with fever or blisters, with or without peeling skin, itching, or swollen lymph nodes, loss of appetite, malaise, nausea, vomiting, abdominal pain, darkened urine, yellowish discoloration of the skin and eyes, light-colored bowel movements, fever, headache, fatigue, myalgias, cough, shortness of breath, chest pain, wheezing, and pain or swelling of the joints.

Patients should be advised to seek medical advice immediately if their symptoms of mycobacterial disease, including, but not limited to, cough, fever, tiredness, shortness of breath, malaise, headache, pain, night sweats, swollen lymph nodes, loss of appetite, weight loss, weakness, skin ulcers or lesions, worsen (see ADVERSE REACTIONS).

Advise patients to abstain from alcohol, hepatotoxic medications or herbal products while taking rifampin.

Compliance with the full course of therapy must be emphasized, and the importance of not missing any doses must be stressed.

Laboratory Tests

Adults treated for tuberculosis with rifampin should have baseline measurements of hepatic enzymes, bilirubin, serum creatinine, a complete blood count, and a platelet count (or estimate). Baseline tests are unnecessary in pediatric patients unless a complicating condition is known or clinically suspected.

Patients should be seen at least monthly during therapy and should be specifically questioned concerning symptoms associated with adverse reactions. All patients with abnormalities should have follow-up, including laboratory testing, if necessary. Routine laboratory monitoring for toxicity in people with normal baseline measurements is generally not necessary.

Drug Interactions

Pharmacodynamic Interactions

Healthy subjects who received rifampin 600 mg once daily concomitantly with saquinavir 1000 mg/ritonavir 100 mg twice daily (ritonavir-boosted saquinavir) developed severe hepatocellular toxicity. Therefore, concomitant use of these medications is contraindicated. (See CONTRAINDICATIONS.)

When rifampin is given concomitantly with other hepatotoxic medications such as halothane or isoniazid, the potential for hepatotoxicity is increased. The concomitant use of rifampin and halothane should be avoided. Patients receiving both rifampin and isoniazid should be monitored closely for hepatotoxicity.

Effect of Rifampin on Other Drugs

Induction of Drug Metabolizing Enzymes and Transporters

Drug metabolizing enzymes and transporters affected by rifampin include cytochromes P450 (CYP) 1A2, 2B6, 2C8, 2C9, 2C19, and 3A4, UDP-glucuronyltransferases (UGT), sulfotransferases, carboxylesterases, and transporters including P-glycoprotein (P-gp) and multidrug resistance-associated protein 2 (MRP2). Most drugs are substrates for one or more of these enzyme or transporter pathways and these pathways may be induced by rifampin simultaneously. Therefore, rifampin may increase the metabolism and decrease the activity of certain coadministered drugs or increase the activity of a coadministered pro-drug (where metabolic activation is required), and has the potential to perpetuate clinically important drug-drug interactions against many drugs and across many drug classes (Table 1).

Table 1 summarizes the effect of rifampin on other drugs or drug classes. Adjust dosages of concomitant drugs based on approved drug labeling and if applicable, therapeutic drug monitoring, unless otherwise specified.

Table 1: Drug Interactions with Rifampin that Affect Concomitant Drug Concentrations [Administered with rifampin 600 mg daily, unless otherwise specified]
Drug or Drug Class and Prevention or Management | Clinical Effect
Antiretrovirals
Prevention or Management: Concomitant use is contraindicated (see CONTRAINDICATIONS)
Atazanavir | Decrease AUC by 72%
Darunavir [Rifampin dosage used concomitantly with the drug(s) is not specified in the proposed package insert.] | Substantial decrease in exposure, which may result in loss of therapeutic effect and development of resistance.
Tipranavir | Substantial decrease in exposure, which may result in loss of therapeutic effect and development of resistance.
Fosamprenavir [Administered with rifampin 300 mg daily] | Decrease AUC by 82%
Saquinavir | Decrease AUC by 70% Coadministration may result in severe hepatocellular toxicity.
Antiretrovirals
Prevention or Management: Avoid concomitant use
Zidovudine | Decrease AUC by 47%
Indinavir | Decrease AUC by 92%
Efavirenz | Decrease AUC by 26%
Cortisol Receptor Blocker
Mifepristone Prevention or Management: Avoid concomitant use | Decrease exposure
Hepatitis C Antiviral
Prevention or Management: Avoid concomitant use
Daclatasvir | Decrease AUC by 79%
Simeprevir | Decrease AUC by 48%
Sofosbuvir | Decrease AUC by 72% Coadministration of sofosbuvir with rifampin may decrease sofosbuvir plasma concentrations, leading to reduced therapeutic effect of sofosbuvir.
Telaprevir | Decrease AUC by 92%
Systemic Hormonal Contraceptives
Prevention or Management: Advise patients to change to non-hormonal methods of birth control during rifampin therapy
Estrogens | Decrease exposure
Progestins | Decrease exposure
Anticonvulsants
Phenytoin [Administered with rifampin 450 mg daily] | Decrease exposure
Antiarrhythmics
Disopyramide | Decrease exposure
Mexiletine | Decrease exposure
Quinidine | Decrease exposure
Propafenone | Decrease AUC by 50%–67%
Tocainide | Decrease exposure
Antiestrogens
Tamoxifen | Decrease AUC by 86%
Toremifene | Decrease steady state concentrations of toremifene in serum
Antithrombotic Agents
Clopidogrel Prevention or Management: Concomitant use of clopidogrel and rifampin should be discouraged | Increase active metabolite exposure and risk of bleeding
Ticagrelor Prevention or Management: Avoid use | Decrease exposure
Antipsychotics
Haloperidol | Decrease plasma concentrations by 70%
Lurasidone Prevention or Management: Concomitant use is contraindicated (See CONTRAINDICATIONS) | Decrease exposure
Oral Anticoagulants
Prevention or Management: Perform prothrombin time daily or as frequently as necessary to establish and maintain the required dose of anticoagulant
Warfarin | Decrease exposure
Antifungals
Fluconazole | Decrease AUC by 23%
Itraconazole Prevention or Management: Not recommended 2 weeks before and during itraconazole treatment | Decrease exposure
Ketoconazole | Decrease exposure
Caspofungin Prevention or Management: Refer to the caspofungin prescribing information for caspofungin dose adjustment. | Decrease exposure
Beta-blockers
Metoprolol | Decrease exposure
Propranolol | Decrease exposure
Benzodiazepines
Diazepam, [Administered with rifampin 1200 mg daily] | Decrease exposure
Benzodiazepine-related drugs
Zopiclone | Decrease AUC by 82%
Zolpidem | Decrease AUC by 73%
Calcium Channel Blockers
Diltiazem | Decrease exposure
Nifedipine [Rifampin 1200 mg administered as a single oral dose 8 hours before administering a single oral dose of nifedipine 10 mg] | Decrease exposure
Verapamil | Decrease exposure
Corticosteroids [Numerous cases in the literature describe a decrease in glucocorticoid effect when used concomitantly with rifampin. The literature contains reports of acute adrenal crisis or adrenal insufficiency induced by the combination of rifampin-isoniazid-ethambutol or rifampin-isoniazid in patients with Addison's disease.]
Prednisolone | Decrease exposure
Cardiac Glycosides
Digoxin Prevention or Management: Measure serum digoxin concentrations before initiating rifampin. Continue monitoring and increase digoxin dose by approximately 20%–40% as necessary. | Decrease exposure
Digitoxin | Decrease exposure
Fluoroquinolones
Pefloxacin [Administered with rifampin 900 mg daily] | Decrease exposure
Moxifloxacin, | Decrease exposure
Oral Hypoglycemic Agents (e.g., sulfonylureas)
Glyburide | Decrease exposure Rifampin may worsen glucose control of glyburide.
Glipizide | Decrease exposure
Immunosuppressive Agents
Cyclosporine | Decrease exposure
Tacrolimus Prevention or Management: Monitoring of whole blood concentrations and appropriate dosage adjustments of tacrolimus are recommended when rifampin and tacrolimus are used concomitantly. | Decrease AUC by 56%
Narcotic Analgesics
Oxycodone | Decrease AUC by 86%
Morphine | Decrease exposure
Progestin Antagonist
Mifepristone Prevention or Management: Refer to the posttreatment assessment in the mifepristone prescribing information to verify that treatment has been successful. | Decrease exposure
Selective 5-HT3 Receptor Antagonists
Ondansetron | Decrease exposure
Statins Metabolized by CYP3A4
Simvastatin | Decrease exposure
Thiazolidinediones
Rosiglitazone | Decrease AUC by 66%
Tricyclic Antidepressants
Nortriptyline [A tuberculosis treatment regimen including rifampin (600 mg/day), isoniazid (300 mg/day), pyrazinamide (500 mg 3× per day), and pyridoxine (25 mg) was associated with higher than expected doses of nortriptyline were required to obtain a therapeutic drug level. Following the discontinuation of rifampin, the patient became drowsy and the serum nortriptyline levels rose precipitously (3-fold) into the toxic range.] | Decrease exposure
Other Drugs
Enalapril | Decrease active metabolite exposure
Chloramphenicol [Concomitant use with rifampin in 2 children] | Decrease exposure
Clarithromycin | Decrease exposure
Dapsone | Rifampin has been shown to increase the clearance of dapsone and, accordingly, decrease dapsone exposure. Rifampin has also been shown to increase the production of the hydroxylamine metabolite of dapsone which could increase the risk of methemoglobinemia.
Doxycycline [Administered with rifampin (10 mg/kg daily)] | Decrease exposure
Irinotecan [Administered with an antibiotic regimen including rifampin (450 mg/day), isoniazid (300 mg/day), and streptomycin (0.5 g/day) IM] Prevention or Management: Avoid the use of rifampin, a strong CYP3A4 inducer, if possible. Substitute non-enzyme inducing therapies at least 2 weeks prior to initiation of irinotecan therapy | Decrease irinotecan and active metabolite exposure
Levothyroxine | Decrease exposure
Losartan | Parent | Decrease AUC by 30%
Losartan | Active metabolite (E3174) | Decrease AUC by 40%
Methadone | In patients well-stabilized on methadone, concomitant administration of rifampin resulted in a marked reduction in serum methadone levels and a concurrent appearance of withdrawal symptoms.
Praziquantel Prevention or Management: Concomitant use is contraindicated (see CONTRAINDICATIONS) | Decrease plasma praziquantel concentrations to undetectable levels.
Quinine Prevention or Management: Avoid concomitant use | Decrease AUC by 75%–85%
Telithromycin | Decrease AUC by 86%
Theophylline | Decrease exposure by 20% to 40%
AUC = area under the time-concentration curve

Effect of Other Drugs on Rifampin

Concomitant antacid administration may reduce the absorption of rifampin. Daily doses of rifampin should be given at least 1 hour before the ingestion of antacids.

Concomitant use with probenecid and cotrimoxazole increases the concentration of rifampin which may increase the risk of RIFADIN toxicities. Monitor for adverse reactions associated with RIFADIN during coadministration.

Other Interactions

Atovaquone: Concomitant use of rifampin with atovaquone decrease concentrations of atovaquone and increase concentrations of rifampin which may increase the risk of RIFADIN toxicities. Coadministration of rifampin with atovaquone is not recommended.

Drug/Laboratory Interactions

Cross-reactivity and false-positive urine screening tests for opiates have been reported in patients receiving rifampin when using the KIMS (Kinetic Interaction of Microparticles in Solution) method (e.g., Abuscreen OnLine opiates assay; Roche Diagnostic Systems). Confirmatory tests, such as gas chromatography/mass spectrometry, will distinguish rifampin from opiates.

Therapeutic levels of rifampin have been shown to inhibit standard microbiological assays for serum folate and vitamin B12. Thus, alternate assay methods should be considered. Transient abnormalities in liver function tests (e.g., elevation in serum bilirubin, alkaline phosphatase, and serum transaminases) and reduced biliary excretion of contrast media used for visualization of the gallbladder have also been observed. Therefore, these tests should be performed before the morning dose of rifampin.

Carcinogenesis, Mutagenesis, Impairment of Fertility

A few cases of accelerated growth of lung carcinoma have been reported in humans, but a causal relationship with the drug has not been established. Hepatomas were increased in female (C3Hf/DP) mice dosed for 60 weeks with rifampin followed by an observation period of 46 weeks, at 20 to 120 mg/kg (equivalent to 0.1 to 0.5 times the maximum dosage used clinically, based on body surface area comparisons). There was no evidence of tumorigenicity in male C3Hf/DP mice or in similar studies in BALB/c mice, or in two-year studies in Wistar rats.

Data from published literature report that rifampin shows mutagenic potential in the Ames test and is considered to be aneugenic as well as clastogenic in vivo in mice after oral administration. Increased frequency of chromosomal aberrations was observed in vitro in lymphocytes obtained from patients treated with combinations of rifampin, isoniazid, and pyrazinamide and combinations of streptomycin, rifampin, isoniazid, and pyrazinamide. The clinical relevance of the nonclinical and in vitro findings is unclear as there is insufficient evidence of carcinogenicity, mutagenicity or impairment of fertility in humans after decades of use of rifampin.

PREGNANCY

Pregnancy–Teratogenic Effects

There are no adequate and well-controlled studies of RIFADIN in pregnant women. Rifampin has been reported to cross the placental barrier and appear in cord blood. While available studies cannot definitively establish the absence of risk, published data over decades of use have not established an association with RIFADIN during pregnancy and major birth defects or miscarriage.

Rifampin has been shown to be teratogenic in rodents. Congenital malformations, primarily spina bifida, were increased in the offspring of pregnant rats given rifampin during organogenesis at oral doses of 150 to 250 mg/kg/day (about 1 to 2 times the maximum recommended human dose based on body surface area comparisons). Cleft palate was increased in a dose-dependent fashion in fetuses of pregnant mice treated at oral doses of 50 to 200 mg/kg (about 0.2 to 0.8 times the maximum recommended human dose based on body surface area comparisons). Imperfect osteogenesis and embryotoxicity were also reported in pregnant rabbits given rifampin at oral doses up to 200 mg/kg/day (about 3 times the maximum recommended human dose based on body surface area comparisons). The clinical relevance of the nonclinical data is uncertain.

Despite the animal findings, it would appear that the possibility of fetal harm is remote, if the drug is used during pregnancy. Nevertheless, because the studies in humans cannot rule out the possibility of harm, RIFADIN should be used during pregnancy only if the potential benefit outweighs the potential risk to the fetus.

Pregnancy–Non-Teratogenic Effects

When administered during the last few weeks of pregnancy, rifampin can cause postnatal hemorrhages in the mother and infant for which treatment with vitamin K may be indicated.

Nursing Mothers

Because of the potential for tumorigenicity shown for rifampin in animal studies, a decision should be made whether to discontinue nursing or discontinue the drug, taking into account the importance of the drug to the mother.

Pediatric Use

See CLINICAL PHARMACOLOGY–Pediatrics; see also DOSAGE AND ADMINISTRATION.

Geriatric Use

Clinical studies of RIFADIN did not include sufficient numbers of subjects aged 65 and over to determine whether they respond differently from younger subjects. Other reported clinical experience has not identified differences in responses between the elderly and younger patients. Caution should therefore be observed in using rifampin in elderly patients. (See WARNINGS.)

ADVERSE REACTIONS

The following adverse reactions associated with the use of RIFADIN were identified in clinical studies or postmarketing reports. Because some of these reactions were reported voluntarily from a population of uncertain size, it is not always possible to reliably estimate their frequency or establish a causal relationship to drug exposure.

Gastrointestinal

Heartburn, epigastric distress, anorexia, nausea, vomiting, jaundice, flatulence, cramps, and diarrhea have been noted in some patients. Although Clostridium difficile has been shown in vitro to be sensitive to rifampin, pseudomembranous colitis has been reported with the use of rifampin (and other broad-spectrum antibiotics). Therefore, it is important to consider this diagnosis in patients who develop diarrhea in association with antibiotic use. Tooth discoloration (which may be permanent) may occur.

Hepatic

Hepatotoxicity including transient abnormalities in liver function tests (e.g., elevations in serum bilirubin, alkaline phosphatase, serum transaminases, gamma-glutamyl transferase), hepatitis, shock-like syndrome with hepatic involvement and abnormal liver function tests, and cholestasis have been reported (see WARNINGS).

Hematologic

Cases of thrombotic microangiopathy, including thrombotic thrombocytopenic purpura and hemolytic uremic syndrome, have been reported (see WARNINGS).

Thrombocytopenia has occurred primarily with high dose intermittent therapy but has also been noted after resumption of interrupted treatment. It rarely occurs during well-supervised daily therapy. This effect is reversible if the drug is discontinued as soon as purpura occurs. Cerebral hemorrhage and fatalities have been reported when rifampin administration has been continued or resumed after the appearance of purpura.

Rare reports of disseminated intravascular coagulation have been observed.

Leukopenia, hemolytic anemia, decreased hemoglobin, bleeding, and vitamin K–dependent coagulation disorders (abnormal prolongation of prothrombin time or low vitamin K–dependent coagulation factors) have been observed.

Agranulocytosis has been reported very rarely.

Central Nervous System

Headache, fever, drowsiness, fatigue, ataxia, dizziness, inability to concentrate, mental confusion, behavioral changes, muscular weakness, pains in extremities, and generalized numbness have been observed.

Psychoses have been rarely reported.

Rare reports of myopathy have also been observed.

Ocular

Visual disturbances have been observed.

Endocrine

Menstrual disturbances have been observed.

Rare reports of adrenal insufficiency in patients with compromised adrenal function have been observed.

Renal

Elevations in BUN and serum uric acid have been reported. Rarely, hemolysis, hemoglobinuria, hematuria, interstitial nephritis, acute tubular necrosis, renal insufficiency, and acute renal failure have been noted. These are generally considered to be hypersensitivity reactions. They usually occur during intermittent therapy or when treatment is resumed following intentional or accidental interruption of a daily dosage regimen, and are reversible when rifampin is discontinued and appropriate therapy instituted.

Dermatologic

Cutaneous reactions are mild and self-limiting and do not appear to be hypersensitivity reactions. Typically, they consist of flushing and itching with or without a rash. More serious cutaneous reactions which may be due to hypersensitivity occur but are uncommon.

Hypersensitivity Reactions

Occasionally, pruritus, urticaria, rash, pemphigoid reaction, erythema multiforme, acute generalized exanthematous pustulosis, Stevens-Johnson syndrome, toxic epidermal necrolysis, drug reaction with eosinophilia and systemic symptoms syndrome (see WARNINGS), vasculitis, eosinophilia, sore mouth, sore tongue, and conjunctivitis have been observed.

Anaphylaxis has been reported rarely.

Respiratory, Thoracic and Mediastinal Disorders

Pulmonary toxicity (including, but not limited to, interstitial lung disease, pneumonitis, hypersensitivity pneumonitis, eosinophilic pneumonia, pulmonary infiltrates, organizing pneumonia, respiratory failure, pulmonary fibrosis, and acute respiratory distress syndrome) has been observed (see WARNINGS).

Miscellaneous

Paradoxical drug reaction has been reported with RIFADIN (see WARNINGS). Edema of the face and extremities has been reported. Other reactions which have occurred with intermittent dosage regimens include "flu syndrome" (such as episodes of fever, chills, headache, dizziness, and bone pain), shortness of breath, wheezing, decrease in blood pressure and shock. The "flu syndrome" may also appear if rifampin is taken irregularly by the patient or if daily administration is resumed after a drug-free interval.

OVERDOSAGE

Signs and Symptoms

Nausea, vomiting, abdominal pain, pruritus, headache, and increasing lethargy will probably occur within a short time after ingestion; unconsciousness may occur when there is severe hepatic disease. Transient increases in liver enzymes and/or bilirubin may occur. Brownish-red or orange discoloration of the skin, urine, sweat, saliva, tears, and feces will occur, and its intensity is proportional to the amount ingested.

Liver enlargement, possibly with tenderness, can develop within a few hours after severe overdosage; bilirubin levels may increase and jaundice may develop rapidly. Hepatic involvement may be more marked in patients with prior impairment of hepatic function. Other physical findings remain essentially normal. A direct effect upon the hematopoietic system, electrolyte levels, or acid-base balance is unlikely.

Facial or periorbital edema has also been reported in pediatric patients. Hypotension, sinus tachycardia, ventricular arrhythmias, seizures, and cardiac arrest were reported in some fatal cases.

Acute Toxicity

The minimum acute lethal or toxic dose is not well established. However, nonfatal acute overdoses in adults have been reported with doses ranging from 9 to 12 gm rifampin. Fatal acute overdoses in adults have been reported with doses ranging from 14 to 60 gm. Alcohol or a history of alcohol abuse was involved in some of the fatal and nonfatal reports. Nonfatal overdoses in pediatric patients ages 1 to 4 years old of 100 mg/kg for one to two doses has been reported.

Treatment

Intensive support measures should be instituted and individual symptoms treated as they arise. The airway should be secured and adequate respiratory exchange established. Since nausea and vomiting are likely to be present, gastric lavage within the first 2 to 3 hours after ingestion is probably preferable to induction of emesis. Following evacuation of the gastric contents, the instillation of activated charcoal slurry into the stomach may help absorb any remaining drug from the gastrointestinal tract. Antiemetic medication may be required to control severe nausea and vomiting.

Active diuresis (with measured intake and output) will help promote excretion of the drug.

For severe cases, extracorporeal hemodialysis may be required. If this is not available, peritoneal dialysis can be used along with forced diuresis.

DOSAGE AND ADMINISTRATION

Rifampin can be administered by the oral route or by IV infusion (see INDICATIONS AND USAGE). IV doses are the same as those for oral.

See CLINICAL PHARMACOLOGY for dosing information in patients with renal failure.

Tuberculosis

Adults: 10 mg/kg, in a single daily administration, not to exceed 600 mg/day, oral or IV

Pediatric Patients: 10–20 mg/kg, not to exceed 600 mg/day, oral or IV

It is recommended that oral rifampin be administered once daily, either 1 hour before or 2 hours after a meal with a full glass of water.

Rifampin is indicated in the treatment of all forms of tuberculosis. A three-drug regimen consisting of rifampin, isoniazid, and pyrazinamide is recommended in the initial phase of short-course therapy which is usually continued for 2 months. The Advisory Council for the Elimination of Tuberculosis, the American Thoracic Society, and the Centers for Disease Control and Prevention recommend that either streptomycin or ethambutol be added as a fourth drug in a regimen containing isoniazid (INH), rifampin, and pyrazinamide for initial treatment of tuberculosis unless the likelihood of INH resistance is very low. The need for a fourth drug should be reassessed when the results of susceptibility testing are known. If community rates of INH resistance are currently less than 4%, an initial treatment regimen with less than four drugs may be considered.

Following the initial phase, treatment should be continued with rifampin and isoniazid for at least 4 months. Treatment should be continued for longer if the patient is still sputum or culture positive, if resistant organisms are present, or if the patient is HIV positive.

Preparation of Solution for IV Infusion

Reconstitute the lyophilized powder by transferring 10 mL of sterile water for injection to a vial containing 600 mg of rifampin for injection. Swirl vial gently to completely dissolve the antibiotic. The reconstituted solution contains 60 mg rifampin per mL and is stable at room temperature for up to 30 hours. Prior to administration, withdraw from the reconstituted solution a volume equivalent to the amount of rifampin calculated to be administered and add to 500 mL of infusion medium. Mix well and infuse at a rate allowing for complete infusion within 3 hours. Alternatively, the amount of rifampin calculated to be administered may be added to 100 mL of infusion medium and infused in 30 minutes.

Dilutions in dextrose 5% for injection (D5W) are stable at room temperature for up to 8 hours and should be prepared and used within this time. Precipitation of rifampin from the infusion solution may occur beyond this time. Dilutions in normal saline are stable at room temperature for up to 6 hours and should be prepared and used within this time. Other infusion solutions are not recommended.

Incompatibilities

Physical incompatibility (precipitate) was observed with undiluted (5 mg/mL) and diluted (1 mg/mL in normal saline) diltiazem hydrochloride and rifampin (6 mg/mL in normal saline) during simulated Y-site administration.

Meningococcal Carriers

Adults: For adults, it is recommended that 600 mg rifampin be administered twice daily for two days.

Pediatric Patients: Pediatric patients 1 month of age or older: 10 mg/kg (not to exceed 600 mg per dose) every 12 hours for two days.

Pediatric patients under 1 month of age: 5 mg/kg every 12 hours for two days.

Preparation of Extemporaneous Oral Suspension

For pediatric and adult patients in whom capsule swallowing is difficult or where lower doses are needed, a liquid suspension may be prepared as follows:

RIFADIN 1% w/v suspension (10 mg/mL) can be compounded using one of four syrups–Simple Syrup (Syrup NF), Simple Syrup (Humco Laboratories), SyrPalta® Syrup (Emerson Laboratories), or Raspberry Syrup (Humco Laboratories).

1. Empty the contents of four RIFADIN 300 mg capsules or eight RIFADIN 150 mg capsules onto a piece of weighing paper.
2. If necessary, gently crush the capsule contents with a spatula to produce a fine powder.
3. Transfer the rifampin powder blend to a 4-ounce amber glass or plastic (high density polyethylene [HDPE], polypropylene, or polycarbonate) prescription bottle.
4. Rinse the paper and spatula with 20 mL of one of the above-mentioned syrups and add the rinse to the bottle. Shake vigorously.
5. Add 100 mL of syrup to the bottle and shake vigorously.

This compounding procedure results in a 1% w/v suspension containing 10 mg rifampin/mL. Stability studies indicate that the suspension is stable when stored at room temperature (25±3°C) or in a refrigerator (2–8°C) for four weeks. This extemporaneously prepared suspension must be shaken well prior to administration.

HOW SUPPLIED

RIFADIN IV (rifampin for injection USP) is available in sterile glass vials containing 600 mg rifampin (NDC 0068-0597-01).

STORAGE AND HANDLING

Storage: Store at 25°C (77°F); excursions permitted to 15–30°C (59–86°F) [see USP Controlled Room Temperature]. Avoid excessive heat (temperatures above 40°C or 104°F). Protect from light.

Rx only

Rifadin IV (rifampin for injection USP) is manufactured by:
sanofi-aventis U.S. LLC
Morristown, NJ 07960
A SANOFI COMPANY

Revised: October 2025

©2025 sanofi-aventis U.S. LLC

PRINCIPAL DISPLAY PANEL - 600 mg Vial Carton

NDC 0068-0597-01
Rx ONLY

Rifadin® IV
rifampin for
injection USP

600mg/vial

For IV Infusion Only

1 Sterile Vial

SANOFI